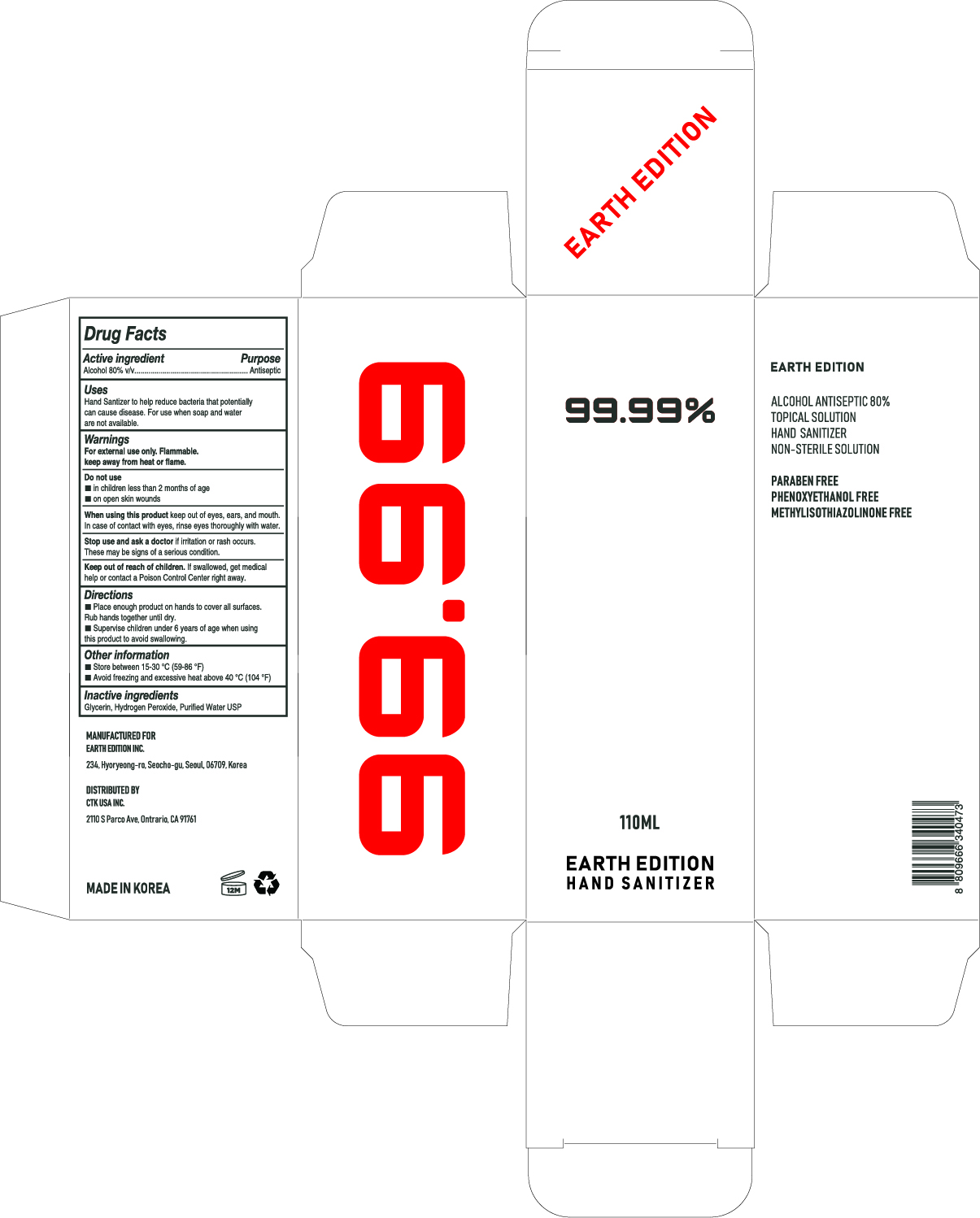 DRUG LABEL: EARTH EDITION HAND SANITIZER
NDC: 76841-1108 | Form: LIQUID
Manufacturer: Earth Edition Inc.
Category: otc | Type: HUMAN OTC DRUG LABEL
Date: 20200510

ACTIVE INGREDIENTS: ALCOHOL 88 mL/110 mL
INACTIVE INGREDIENTS: GLYCERIN; HYDROGEN PEROXIDE; WATER

EARTH EDITION HAND SANITIZER
110 mL
76841-1108-2